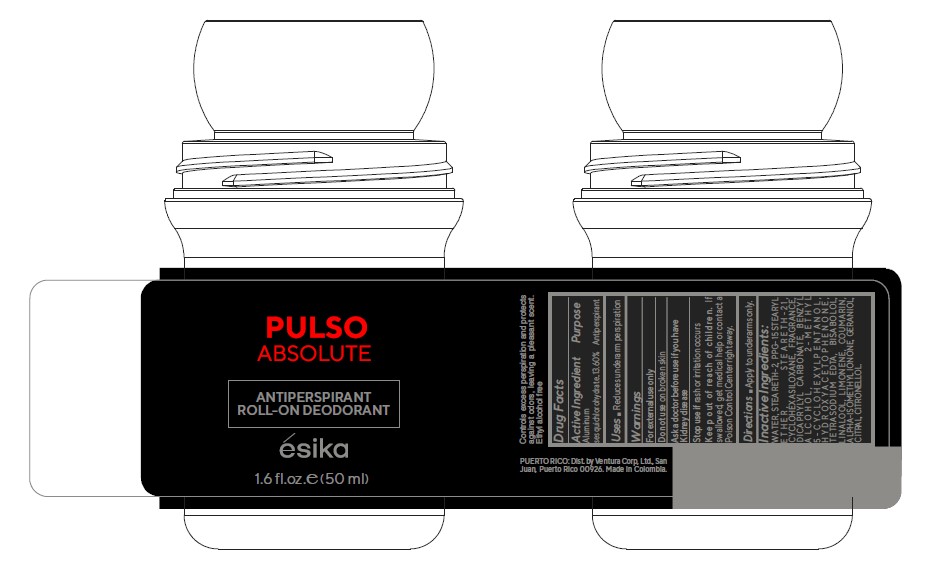 DRUG LABEL: Pulso Absolute Antiperspirant Roll-on Deodorant
NDC: 14141-214 | Form: EMULSION
Manufacturer: Bel Star S.A. (Colombia)
Category: otc | Type: HUMAN OTC DRUG LABEL
Date: 20241028

ACTIVE INGREDIENTS: ALUMINUM SESQUICHLOROHYDRATE 13.6 g/100 mL
INACTIVE INGREDIENTS: GERANIOL; CITRAL; .BETA.-CITRONELLOL, (R)-; STEARETH-21; CYCLOMETHICONE 6; HYDROXYACETOPHENONE; EDETATE SODIUM; LEVOMENOL; COUMARIN; BENZYL ALCOHOL; LINALOOL, (+/-)-; STEARETH-2; PPG-15 STEARYL ETHER; LIMONENE, (+)-; DICAPRYLYL CARBONATE; ISOMETHYL-.ALPHA.-IONONE; WATER

Pulso Absolute Antiperspirant Roll-on Deodorant

Active Ingredient Purpose
Aluminum sesquichlorohydrate 13.60% Antiperspirant

Uses

- Reduces underarm perspiration

Keep out of reach of children. If Swallowed, get medical help or contact a Poison Control Center right away.

Stop use if rash or irritation occurs.

Warnings
For external use only
Do not use on broken skin
Ask a doctor before use if you have kidney disease

Directions
Apply to underarms only.

INACTIVE INGREDIENT

Inactive ingredients: WATER, STEARETH-2, PPG-15 STEARYL ETHER, STEARETH-21, CYCLOHEXASILOXANE, FRAGRANCE, DICAPRYLYL CARBONATE, BENZYL ALCOHOL, 2-METHYL 5-CYCLOHEXYLPENTANOL, HYDROXYACETOPHENONE, TETRASODIUM EDTA, BISABOLOL, LINALOOL, LIMONENE, COUMARIN, ALPHA-ISOMETHYL IONONE, GERANIOL, CITRAL, CITRONELLOL.

PACKAGE LABEL

Pulso Absolute

Antiperspirant Roll-on Deodorant

esika

1.6 fl.oz. (50ml)